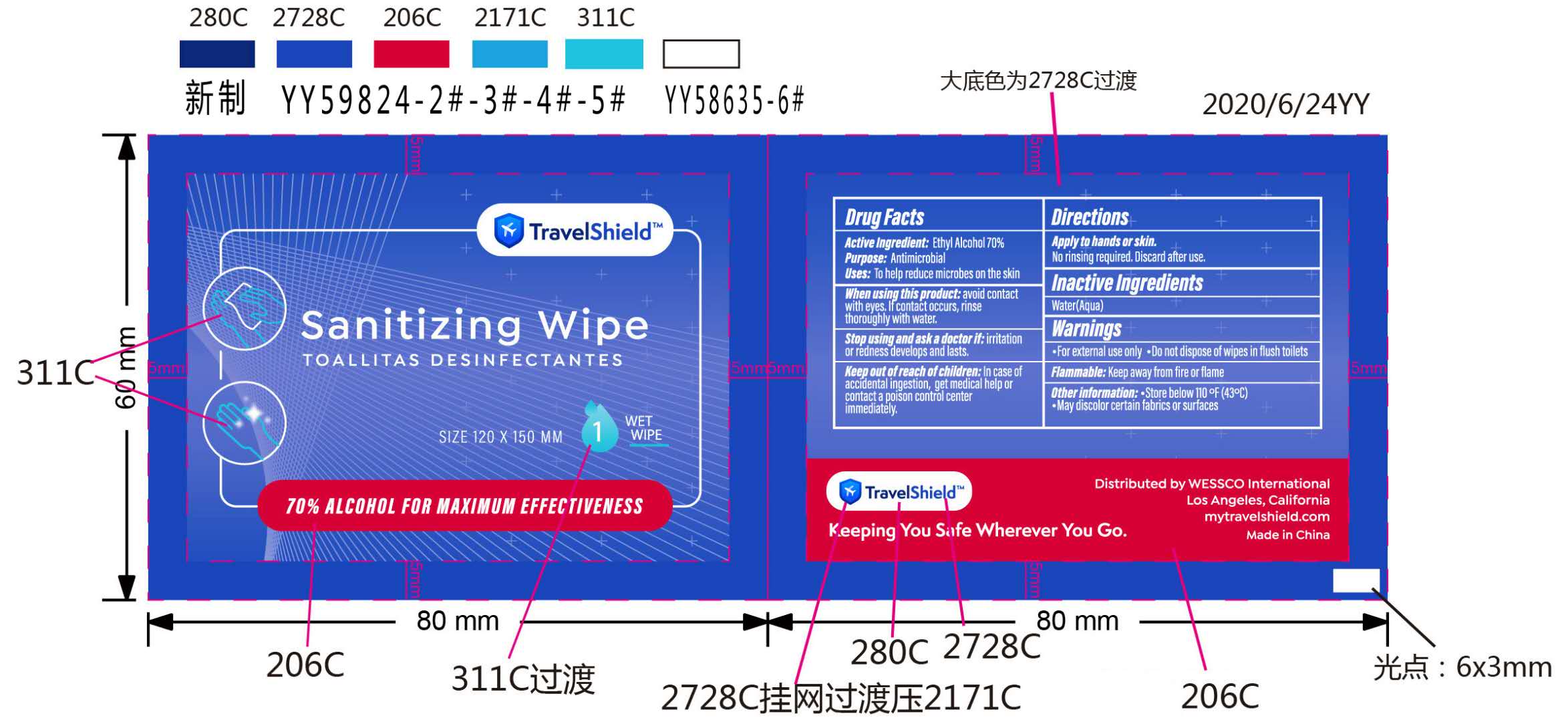 DRUG LABEL: TRAVELSHIELD SANITIZING WIPE (70% Alcohol)
NDC: 96285-002 | Form: CLOTH
Manufacturer: Yangzhou Zhouwan Medical Devices Co.,Ltd
Category: otc | Type: HUMAN OTC DRUG LABEL
Date: 20201109

ACTIVE INGREDIENTS: ALCOHOL 70 mL/100 mL
INACTIVE INGREDIENTS: WATER

Yangzhou Zhouwan Medical Devices Co.,Ltd
TRAVELSHIELD SANITIZING WIPE (70% Alcohol)
75pcs 96285-002-01
20pcs 96285-002-02

Active Ingredient(s)

Ethyl Alcohol 70%

Purpose

Antimicrobial

Use

To help reduce microbes on the skin.

Warnings

- For external use only.
- Do not dispose of wipes in flush toilets.
- Flammable: Keep away from fire or flame.

When using this product: avoid contact with eyes. lf contact occurs, rinse thoroughly with water.

STOP USE

Stop using and ask a doctor if: irritation or redness develops and lasts.

Keep out of reach of children: ln case of accidental ingestion, get medical help or contact a poison control center immediately.

Directions

- Apply to hands or skin.
- No rinsing required.
- Discard after use.

Other information

- Store below 110 °F（43° C).
- May discolor certain fabrics or surfaces.

Inactive ingredients

Water(Aqua).

Package Label - Principal Display Panel

75pcs NDC: 96285-002-01

20pcs NDC: 96285-002-02